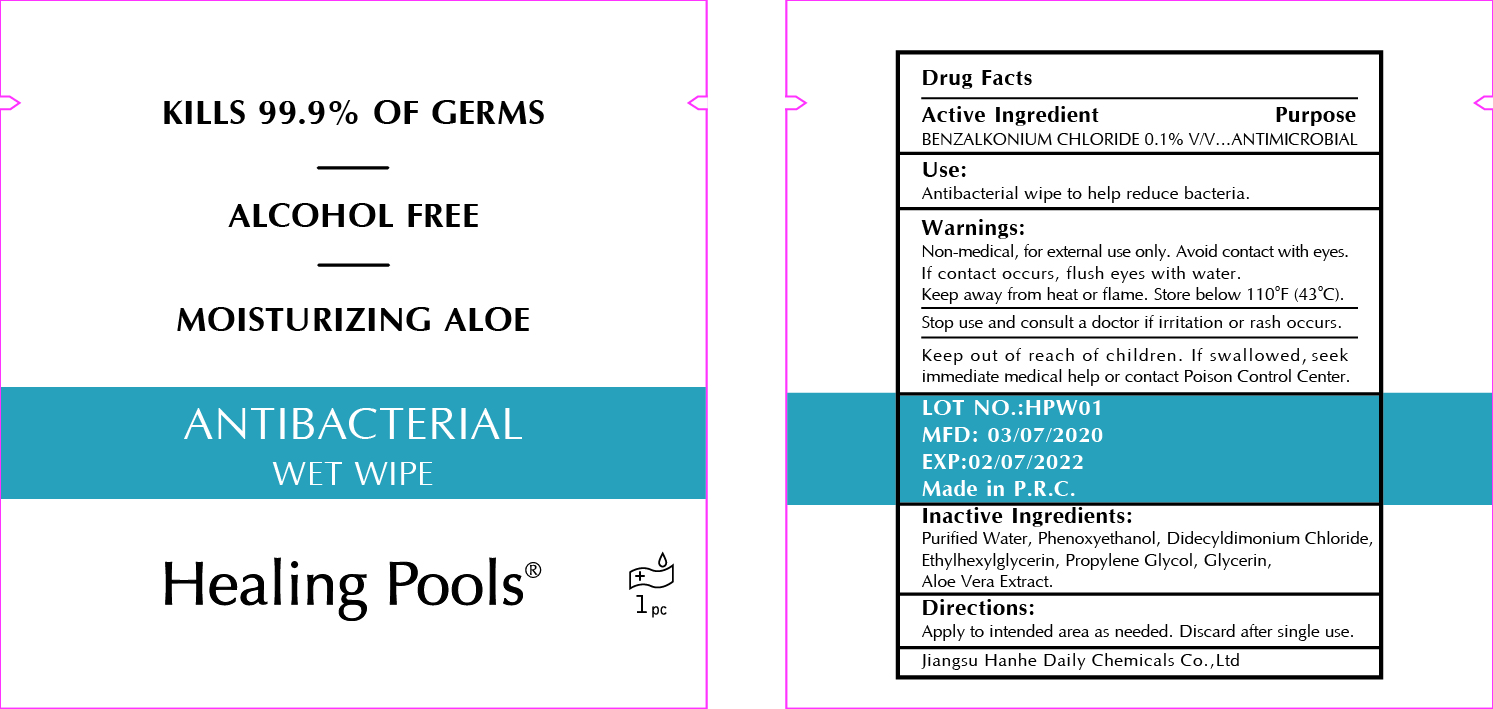 DRUG LABEL: Healing Pools Moisturizing Aloe Antibacterial Wet Wipe
NDC: 73027-214 | Form: SOLUTION
Manufacturer: JIANGSU HANHE DAILY CHEMICALS CO., LTD.
Category: otc | Type: HUMAN OTC DRUG LABEL
Date: 20211102

ACTIVE INGREDIENTS: BENZALKONIUM CHLORIDE 1.7 mg/1 1
INACTIVE INGREDIENTS: GLYCERIN; ETHYLHEXYLGLYCERIN; WATER; PHENOXYETHANOL; PROPYLENE GLYCOL; DIDECYLDIMONIUM CHLORIDE; ALOE VERA WHOLE

-214 healing pools

Active Ingredient

Benzalkonium Chloride 0.1%

Purpose

Antimicrobial

Use

Antibacterial wipe to help reduce bacteria

Warnings

Non Medical. For external use only.

Keep away from heat or flame

Avoid contact with eyes. If contact occurs, flush eyes with water

Stop use and consult a doctor if irritation or rash occurs.

Keep out of reach of children. If swallowed, seek immediate medical help or contact a poison control center

Directions

- Apply to intended area as needed. Discard after single use

Other Information

Store below 110F (43C)

Inactive ingredients

Water, Glycerin, Phenoxyethanol, Didecyldimonium Chloride, Ethylhexylglycerin, Propylene Glycol, Aloe Vera Extract